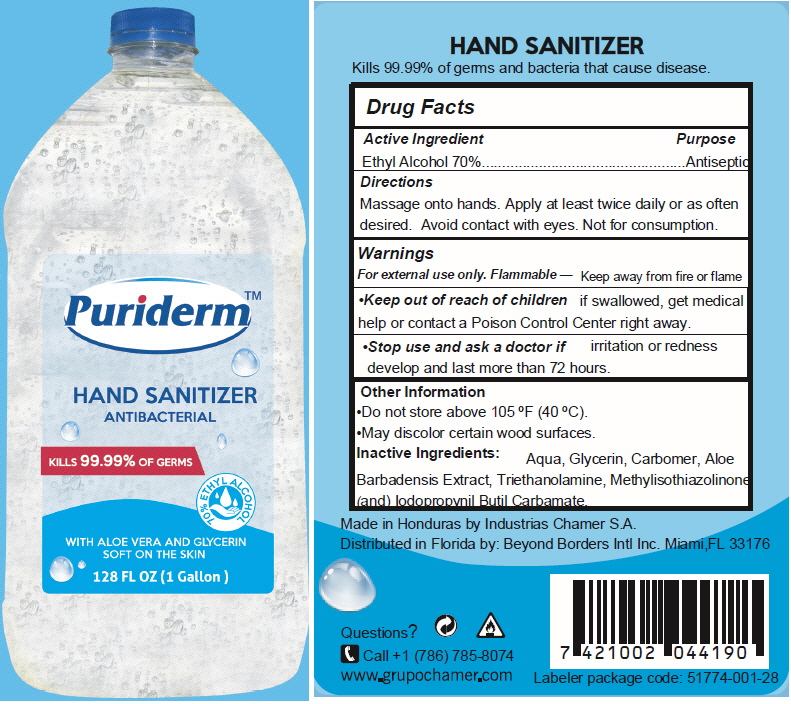 DRUG LABEL: Hand Sanitizer
NDC: 77896-001 | Form: GEL
Manufacturer: Beyond Borders Intl
Category: otc | Type: HUMAN OTC DRUG LABEL
Date: 20200625

ACTIVE INGREDIENTS: Alcohol 70 mL/100 mL
INACTIVE INGREDIENTS: WATER; GLYCERIN; CARBOMER HOMOPOLYMER, UNSPECIFIED TYPE; ALOE VERA LEAF; TROLAMINE; METHYLISOTHIAZOLINONE; IODOPROPYNYL BUTYLCARBAMATE

Puriderm™ HAND SANITIZER

Drug Facts

Active Ingredient

Ethyl Alcohol 70%

INDICATIONS AND USAGE

Purpose

Antiseptic

Directions

Massage onto hands. Apply at least twice daily or as often as desired. Avoid contact with eyes. Not for consumption.

Warnings

For external use only. Flammable – Keep away from fire or flame

- Keep out of reach of children if swallowed, get medical help or contact a Poison Control Center right away.

- Stop use and ask a doctor if irritation or redness develop and last more than 72 hours.

Other Information

- Do not store above 105 °F (40 °C).
- May discolor certain wood surfaces.

Inactive Ingredients

Aqua, Glycerin, Carbomer, Aloe Barbadensis Extract, Triethanolamine, Methylisothiazolinone (and) lodopropynil Butil Carbamate.

Questions?

Call +1 (786) 785-8074

Distributed in Florida by: Beyond Borders Intl Inc. Miami,FL 33176

PRINCIPAL DISPLAY PANEL - 1 Gallon Bottle

Puriderm™

HAND SANITIZER
ANTIBACTERIAL

KILLS 99.99% OF GERMS

70% ETHYL ALCOHOL

WITH ALOE VERA AND GLYCERIN
SOFT ON THE SKIN

128 FL OZ (1 Gallon)